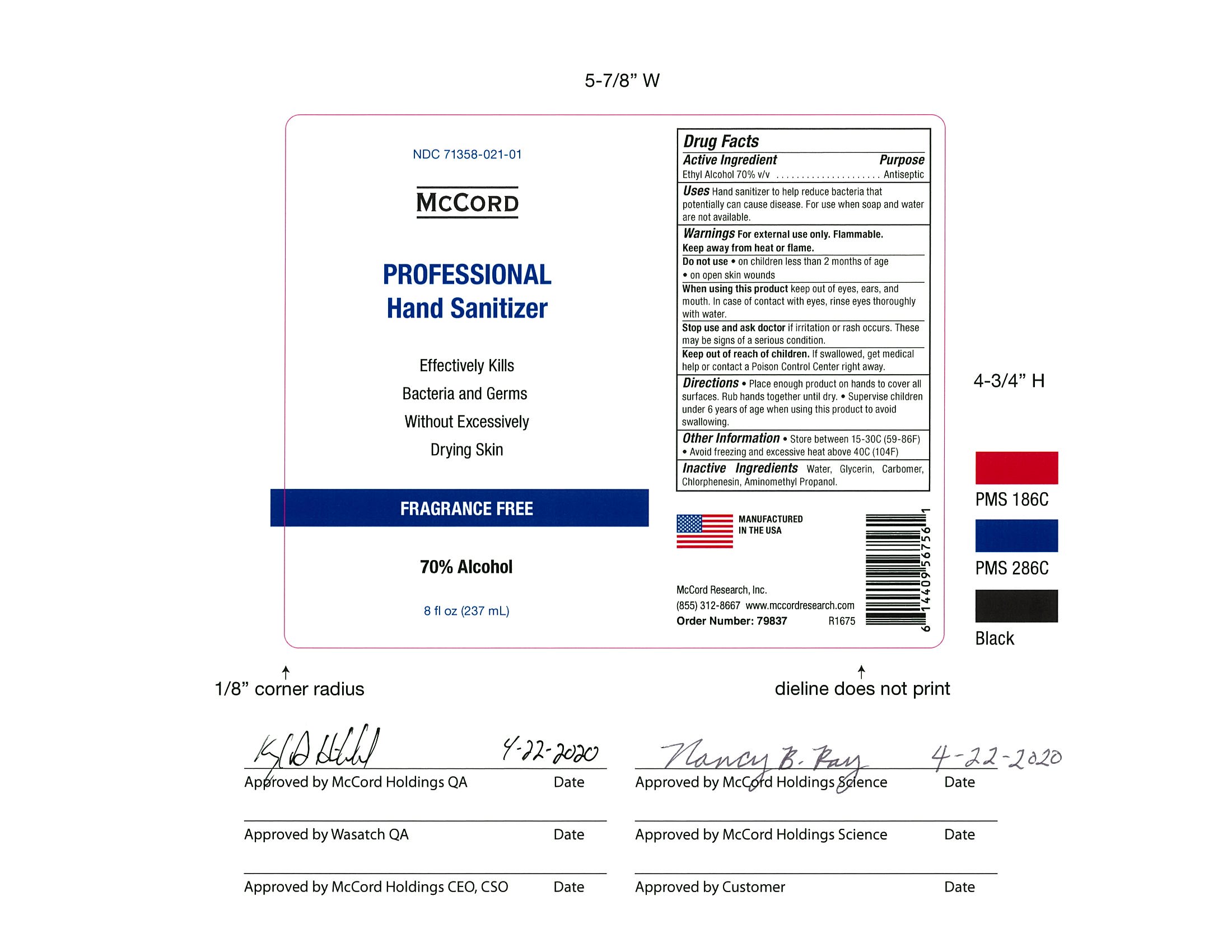 DRUG LABEL: McCord Professional Hand Sanitizer
NDC: 71358-021 | Form: GEL
Manufacturer: McCord Research
Category: otc | Type: HUMAN OTC DRUG LABEL
Date: 20220125

ACTIVE INGREDIENTS: ALCOHOL 70 mL/100 mL
INACTIVE INGREDIENTS: WATER; CARBOMER HOMOPOLYMER, UNSPECIFIED TYPE; CHLORPHENESIN; GLYCERIN; AMINOMETHYLPROPANOL

McCord Professional Hand Sanitizer

ACTIVE INGREDIENT

Alcohol 70% v/v

Purpose

Antiseptic

Use

Hand Sanitizer to help reduce bacteria that potentially can cause disease. For use when soap and water are

not available.

Warnings

For external use only. Flammable. Keep away from heat or flame.

Do Not Use

• on children less than 2 months of age

• on open skin wounds

When Using

When using this product keep out of eyes, ears, and mouth. In case of contact with eyes, rinse eyes

thoroughly with water.

Stop Use

Stop use and ask a doctor if irritation or rash occurs. These may be signs of a serious condition.

Keep out of reach of children. If swallowed, get medical help or contact a Poison Control Center right

away.

Inactive Ingredients

Aminomethyl Propanol, Carbomer, Chlorphenesin, Glycerin, Water

Directions

• Place enough product on hands to cover all surfaces. Rub hands together until dry.

• Supervise children under 6 years of age when using this product to avoid swallowing.

Other Information

• Store between 15-30C (59-86F).

• Avoid freezing and excessive heat above 40C (104F).

Directions

• Place enough product on hands to cover all surfaces. Rub hands together until dry.

• Supervise children under 6 years of age when using this product to avoid swallowing.